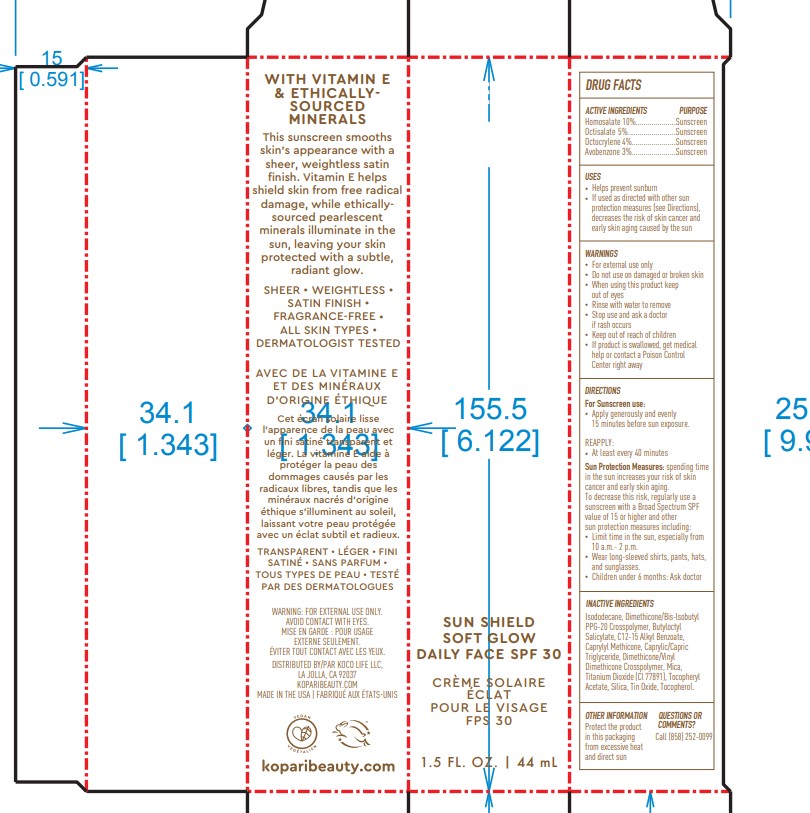 DRUG LABEL: KOPARI Sun Shield Soft Glow Daily Face SPF30
NDC: 68577-153 | Form: SPRAY
Manufacturer: COSMAX USA, CORPORATION
Category: otc | Type: HUMAN OTC DRUG LABEL
Date: 20241226

ACTIVE INGREDIENTS: AVOBENZONE 3 mg/100 mg; HOMOSALATE 10 mg/100 mg; OCTOCRYLENE 4 mg/100 mg; OCTISALATE 5 mg/100 mg
INACTIVE INGREDIENTS: ISODODECANE; DIMETHICONE/BIS-ISOBUTYL PPG-20 CROSSPOLYMER; BUTYLOCTYL SALICYLATE; ALKYL (C12-15) BENZOATE; CAPRYLYL TRISILOXANE; MEDIUM-CHAIN TRIGLYCERIDES; DIMETHICONE/VINYL DIMETHICONE CROSSPOLYMER (SOFT PARTICLE); MICA; TITANIUM DIOXIDE; .ALPHA.-TOCOPHEROL ACETATE; SILICON DIOXIDE; STANNOUS OXIDE; TOCOPHEROL; PHENOXYETHANOL

KOPARI Sun Shield Soft Glow Daily Face SPF30

Active Ingredients

Homosalate 10%

Octisalate 5%

Octocrylene 4%

Avobenzone 3%

Purpose

Sunscreen

USES

- helps prevent sunburn
- if used as directed with other sun protection measures (see Directions), decreases the risk of skin cancer and early skin aging cause by the sun

Warnings

For extenal use only

Do not useon damaged or broken skin

WHEN USING

When using this productkeep out of eyes. Rinse with water to remove.

Stop use and ask a doctor ifrash occurs

Keep out of reach of children.If swallowed, get medical help or contact a Poison Control Center right away.

DIRECTIONS

- Apply generously and evenly 15 minutes before sun exposure
  - Reapply At least every 40 minutes
  - Sun Protection Measures. Spending time in the sun increases your risk of skin cancer and early skin aging. To decrease this risk, regularly use a sunscreen with a Broad Spectrum SPF value of 15 or higher and other sun protection measures including:

- limit time in the sun, especially from 10 a.m. - 2p.m.

-wear long-sleeved shirts, pants, hats and sunglasses

Children under 6 months of age: Ask a doctor

INACTIVE INGREDIENT

Inactive ingredients:Isododecane, Dimethicone/Bis-lsobutyl PPG-20 Crosspolymer, Butyloctyl Salicylate, C12-15 Alkyl Benzoate, Caprylyl Methicone, Caprylic/Capric Triglyceride, Dimethicone/Vinyl Dimethicone Crosspolymer, Mica, Titanium Dioxide (Cl 77891), Tocopheryl Acetate, Silica, Tin Oxide, Tocopherol.

OTHER INFORMATION

- Protect the product in this container from excessive heat and direct sun

QUESTIONS or COMMENTS

Call (858) 252 0099

PACKAGE LABEL

Packaging